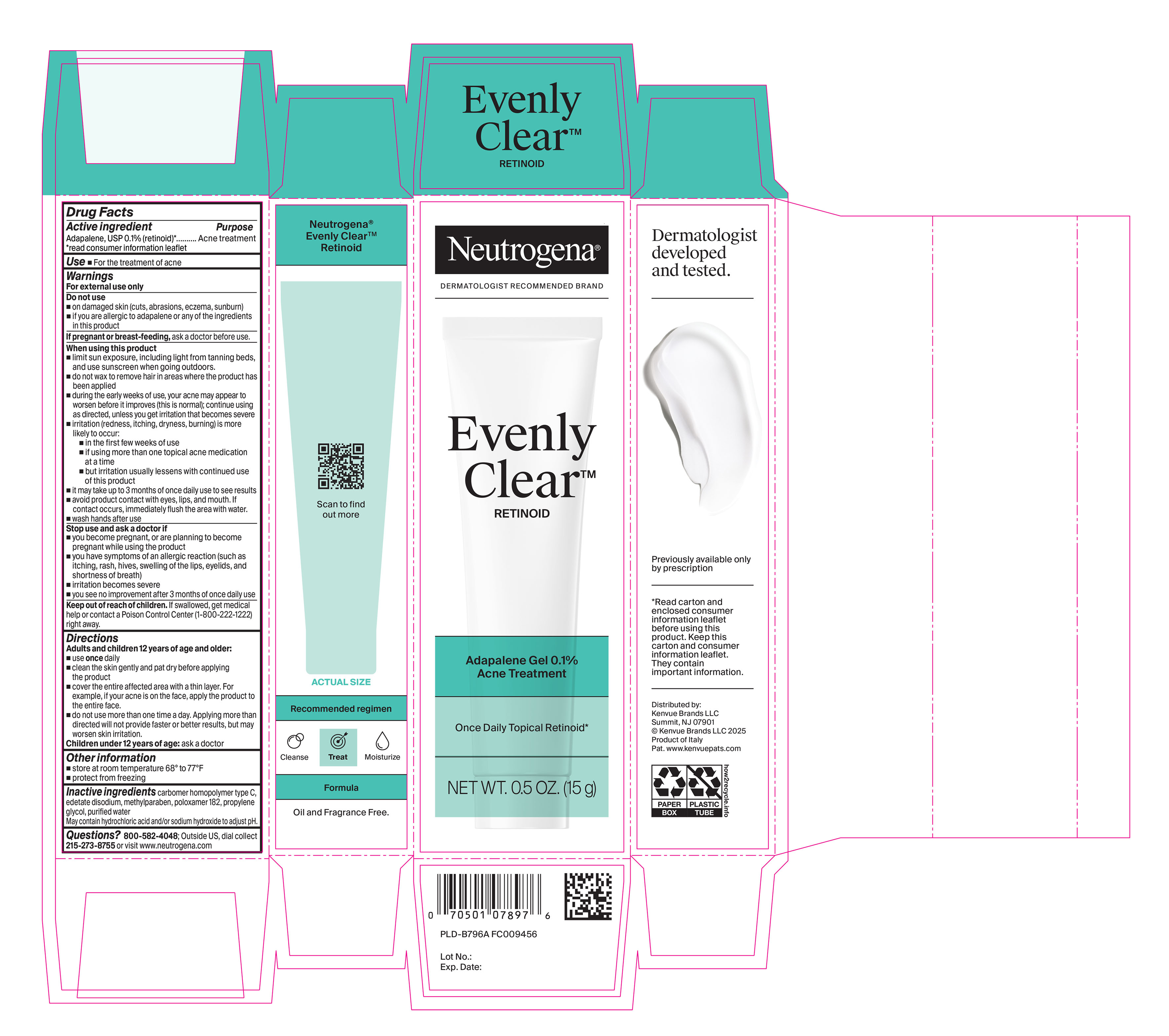 DRUG LABEL: Neutrogena Evenly Clear Retinoid Adapalene Gel 0.1% Acne Treatment
NDC: 69968-0945 | Form: GEL
Manufacturer: Kenvue Brands LLC
Category: otc | Type: HUMAN OTC DRUG LABEL
Date: 20251001

ACTIVE INGREDIENTS: ADAPALENE 1 mg/1 g
INACTIVE INGREDIENTS: CARBOMER HOMOPOLYMER TYPE C; EDETATE DISODIUM; METHYLPARABEN; POLOXAMER 182; PROPYLENE GLYCOL; WATER; HYDROCHLORIC ACID; SODIUM HYDROXIDE

Neutrogena Evenly Clear Retinoid Adapalene Gel 0.1% Acne Treatment

Drug Facts

Active Ingredient

Adapalene, USP 0.1% (retinoid)*

*read consumer information leaflet

Purpose

Acne treatment

Use

For the treatment of acne.

Warnings

For external use only

Do not use

▪on damaged skin (cuts, abrasions, eczema, sunburn)

▪ if you are allergic to adapalene or any of the ingredients in this product

PREGNANCY OR BREAST FEEDING

If pregnant or breast-feeding, ask a doctor before use.

When using this product

- limit sun exposure, including light from tanning beds, and use sunscreen when going outdoors.
- do not wax to remove hair in areas where the product has been applied
- during the early weeks of use, your acne may appear to worsen before it improves (this is normal); continue using as directed, unless you get irritation that becomes severe
- irritation (redness, itching, dryness, burning) is more likely to occur:
- in the first few weeks of use
- if using more than one topical acne medication at a time
- but irritation usually lessens with continued use of this product
- it may take up to 3 months of once daily use to see results
- avoid product contact with eyes, lips, and mouth. If contact occurs, immediately flush the area with water.
- wash hands after use

Stop use and ask a doctor if

▪you become pregnant, or are planning to become pregnant while using the product

▪ you have symptoms of an allergic reaction (such as itching, rash, hives, swelling of the lips, eyelids, and

shortness of breath)

▪ irritation becomes severe

▪ you see no improvement after 3 months of once daily use

Keep out of reach of children. If swallowed, get medical help or contact a Poison Control Center (1-800-222-1222) right away.

Directions

Adults and children 12 years of age and older:

▪ use once daily

▪ clean the skin gently and pat dry before applying

the product

▪ cover the entire affected area with a thin layer. For example, if your acne is on the face, apply the product to

the entire face.

▪ do not use more than one time a day. Applying more than directed will not provide faster or better results, but may worsen skin irritation.

Children under 12 years of age: ask a doctor

Other Information

▪ store at room temperature 68° to 77°F

▪ protect from freezing

Inactive Ingredients

carbomer homopolymer type C, edetate disodium, methylparaben, poloxamer 182, propylene glycol, purified water

May contain hydrochloric acid and/or sodium hydroxide to adjust pH.

Questions?

800-582-4048; Outside US, dial collect 215-273-8755 or visit www.neutrogena.com

Distributed by:

Kenvue Brands LLC

Summit, NJ 07901

PRINCIPAL DISPLAY PANEL - 15g Tube in Carton Label

Neutrogena®

DERMATOLOGIST RECOMMENDED BRAND

Evenly

ClearTM

RETINOID

Adapalene Gel 0.1%

Acne Treatment

Once Daily Topical Retinoid*

NET WT. 0.5 OZ. (15 g)